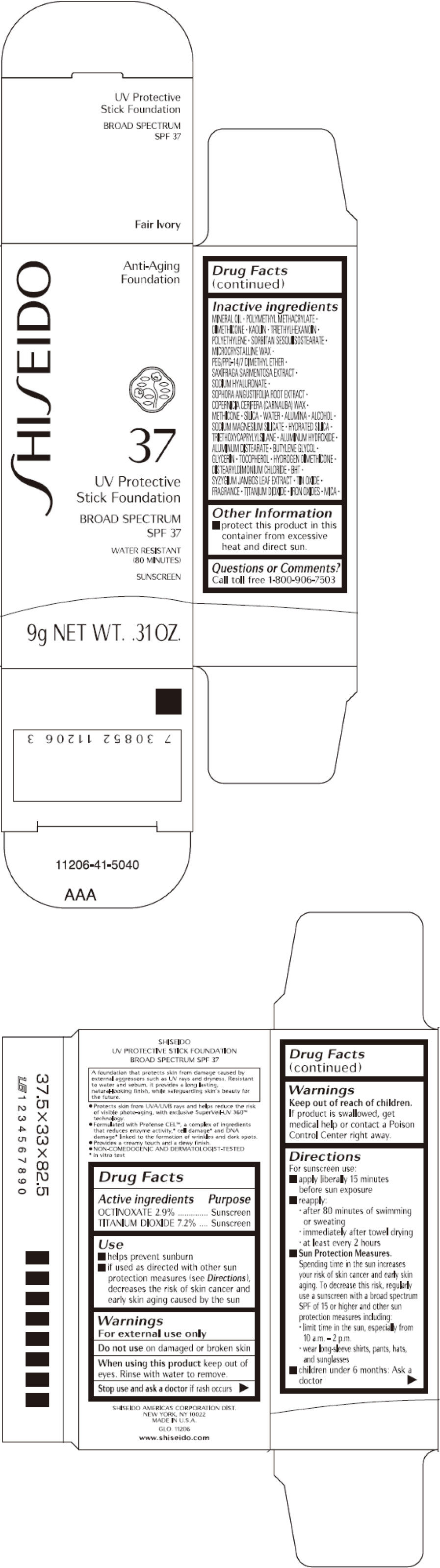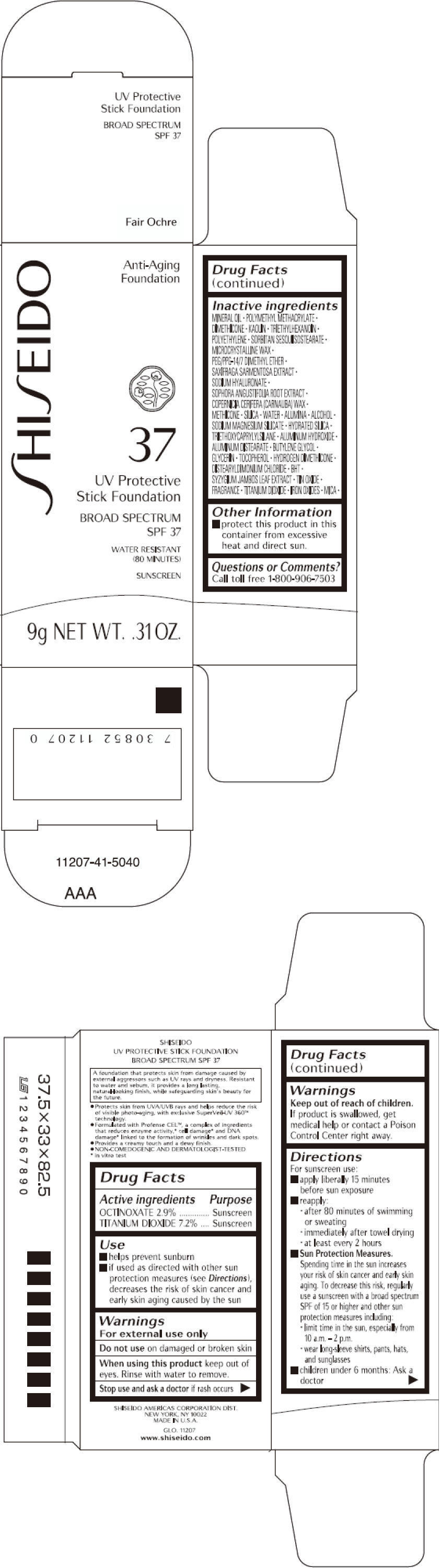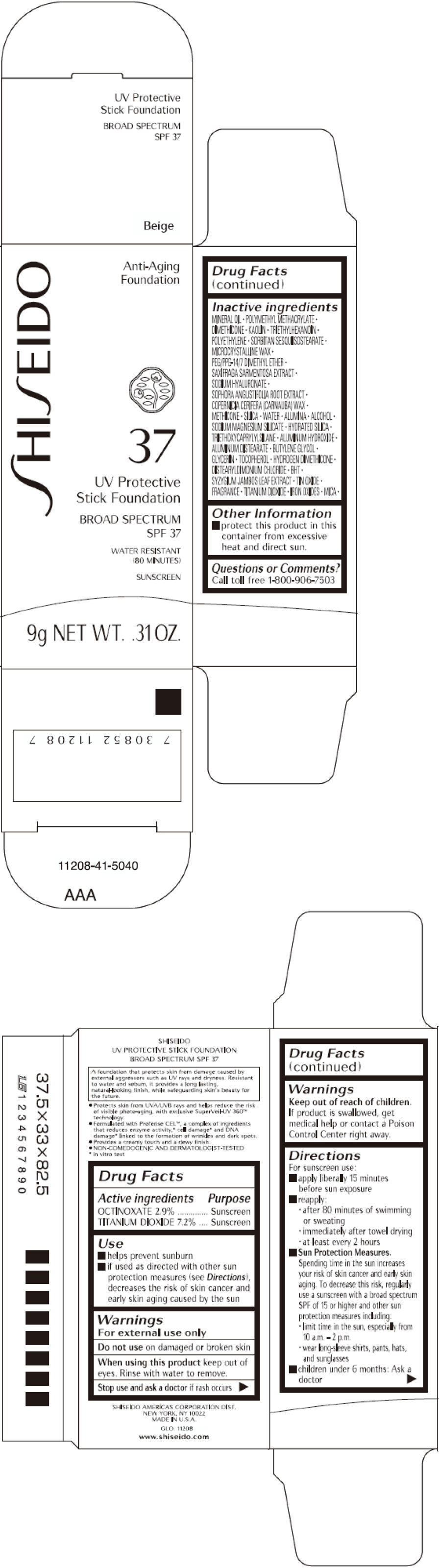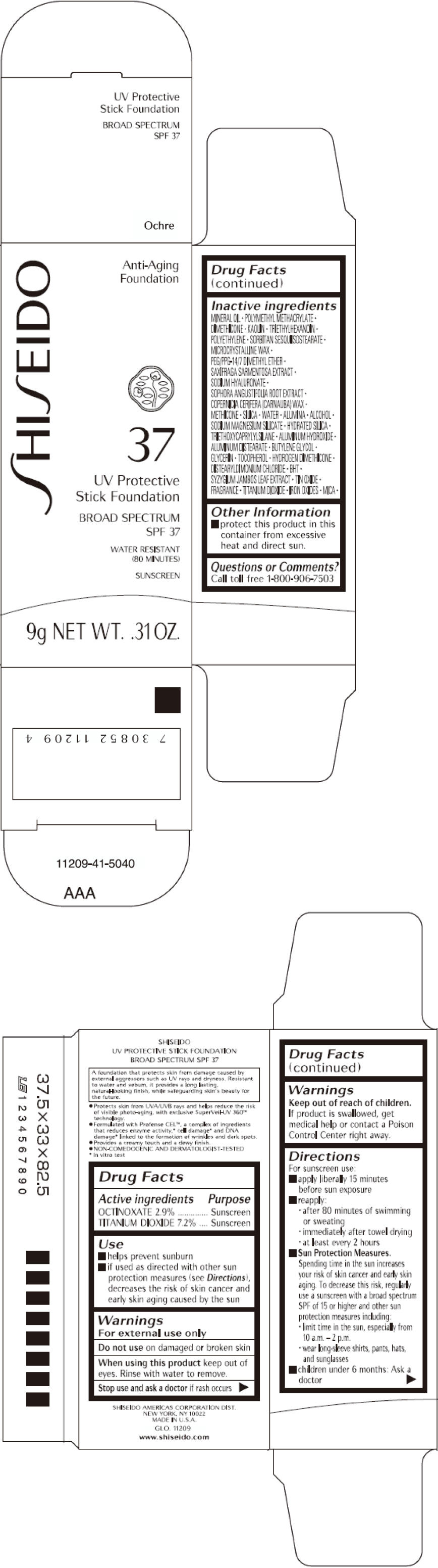 DRUG LABEL: SHISEIDO UV PROTECTIVE FOUNDATION

NDC: 58411-137 | Form: STICK
Manufacturer: SHISEIDO AMERICAS CORPORATION
Category: otc | Type: HUMAN OTC DRUG LABEL
Date: 20260105

ACTIVE INGREDIENTS: OCTINOXATE 261 mg/9 g; TITANIUM DIOXIDE 648 mg/9 g
INACTIVE INGREDIENTS: MINERAL OIL; DIMETHICONE; KAOLIN; TRIETHYLHEXANOIN; HIGH DENSITY POLYETHYLENE; MICROCRYSTALLINE WAX; PEG/PPG-14/7 DIMETHYL ETHER; SAXIFRAGA STOLONIFERA LEAF; HYALURONATE SODIUM; SOPHORA FLAVESCENS ROOT; CARNAUBA WAX; METHICONE (20 CST); SILICON DIOXIDE; WATER; ALUMINUM OXIDE; ALCOHOL; HYDRATED SILICA; TRIETHOXYCAPRYLYLSILANE; ALUMINUM HYDROXIDE; ALUMINUM DISTEARATE; BUTYLENE GLYCOL; GLYCERIN; TOCOPHEROL; DISTEARYLDIMONIUM CHLORIDE; BUTYLATED HYDROXYTOLUENE; SYZYGIUM JAMBOS LEAF; STANNIC OXIDE; FERRIC OXIDE RED; FERRIC OXIDE YELLOW; FERROSOFERRIC OXIDE; MICA

SHISEIDO UV PROTECTIVE FOUNDATION

Drug Facts

ACTIVE INGREDIENT

Active ingredients | Purpose
OCTINOXATE 2.9% | Sunscreen
TITANIUM DIOXIDE 7.2% | Sunscreen

Uses

- helps prevent sunburn
- if used as directed with other sun protection measures (see Directions), decreases the risk of skin cancer and early skin aging caused by the sun

Warnings

For external use only

Do not useon damaged or broken skin

WHEN USING

When using this productkeep out of eyes. Rinse with water to remove.

Stop use and ask a doctorif rash occurs

Keep out of reach of children.If product is swallowed, get medical help or contact a Poison Control Center right away.

Directions

For sunscreen use:

- apply liberally 15 minutes before sun exposure
- reapply:
  - after 80 minutes of swimming or sweating
  - immediately after towel drying
  - at least every 2 hours
- Sun Protection Measures. Spending time in the sun increases your risk of skin cancer and early skin aging. To decrease this risk, regularly use a sunscreen with a broad spectrum SPF of 15 or higher and other sun protection measures including:
  - limit time in the sun, especially from 10 a.m. – 2 p.m.
  - wear long-sleeve shirts, pants, hats, and sunglasses
- children under 6 months: Ask a doctor

Inactive Ingredients

MINERAL OIL, POLYMETHYL METHACRYLATE, DIMETHICONE, KAOLIN, TRIETHYLHEXANOIN, POLYETHYLENE, SORBITAN SESQUIISOSTEARATE, MICROCRYSTALLINE WAX, PEG/PPG-14/7 DIMETHYL ETHER, SAXIFRAGA SARMENTOSA EXTRACT, SODIUM HYALURONATE, SOPHORA ANGUSTIFOLIA ROOT EXTRACT, COPERNICIA CERIFERA (CARNAUBA) WAX, METHICONE, SILICA, WATER, ALUMINA, ALCOHOL, SODIUM MAGNESIUM SILICATE, HYDRATED SILICA, TRIETHOXYCAPRYLYLSILANE, ALUMINUM HYDROXIDE, ALUMINUM DISTEARATE, BUTYLENE GLYCOL, GLYCERIN, TOCOPHEROL, HYDROGEN DIMETHICONE, DISTEARYLDIMONIUM CHLORIDE, BHT, SYZYGIUM JAMBOS LEAF EXTRACT, TIN OXIDE, FRAGRANCE, TITANIUM DIOXIDE, IRON OXIDES, MICA,

Other information

- protect this product in this container from excessive heat and direct sun.

Questions or comments?

Call toll free 1-800-906-7503

PRINCIPAL DISPLAY PANEL - 9 g Cartridge Carton - Fair Ivory

SHI SEIDO

Anti-Aging
Foundation

37

UV Protective
Stick Foundation

BROAD SPECTRUM
SPF 37

WATER RESISTANT
(80 MINUTES)

SUNSCREEN

9g NET WT. .31 OZ.

PRINCIPAL DISPLAY PANEL - 9 g Cartridge Carton - Fair Ochre

SHI SEIDO

Anti-Aging
Foundation

37

UV Protective
Stick Foundation

BROAD SPECTRUM
SPF 37

WATER RESISTANT
(80 MINUTES)

SUNSCREEN

9g NET WT. .31 OZ.

PRINCIPAL DISPLAY PANEL - 9 g Cartridge Carton - Beige

SHI SEIDO

Anti-Aging
Foundation

37

UV Protective
Stick Foundation

BROAD SPECTRUM
SPF 37

WATER RESISTANT
(80 MINUTES)

SUNSCREEN

9g NET WT. .31 OZ.

PRINCIPAL DISPLAY PANEL - 9 g Cartridge Carton - Ochre

SHI SEIDO

Anti-Aging
Foundation

37

UV Protective
Stick Foundation

BROAD SPECTRUM
SPF 37

WATER RESISTANT
(80 MINUTES)

SUNSCREEN

9g NET WT. .31 OZ.